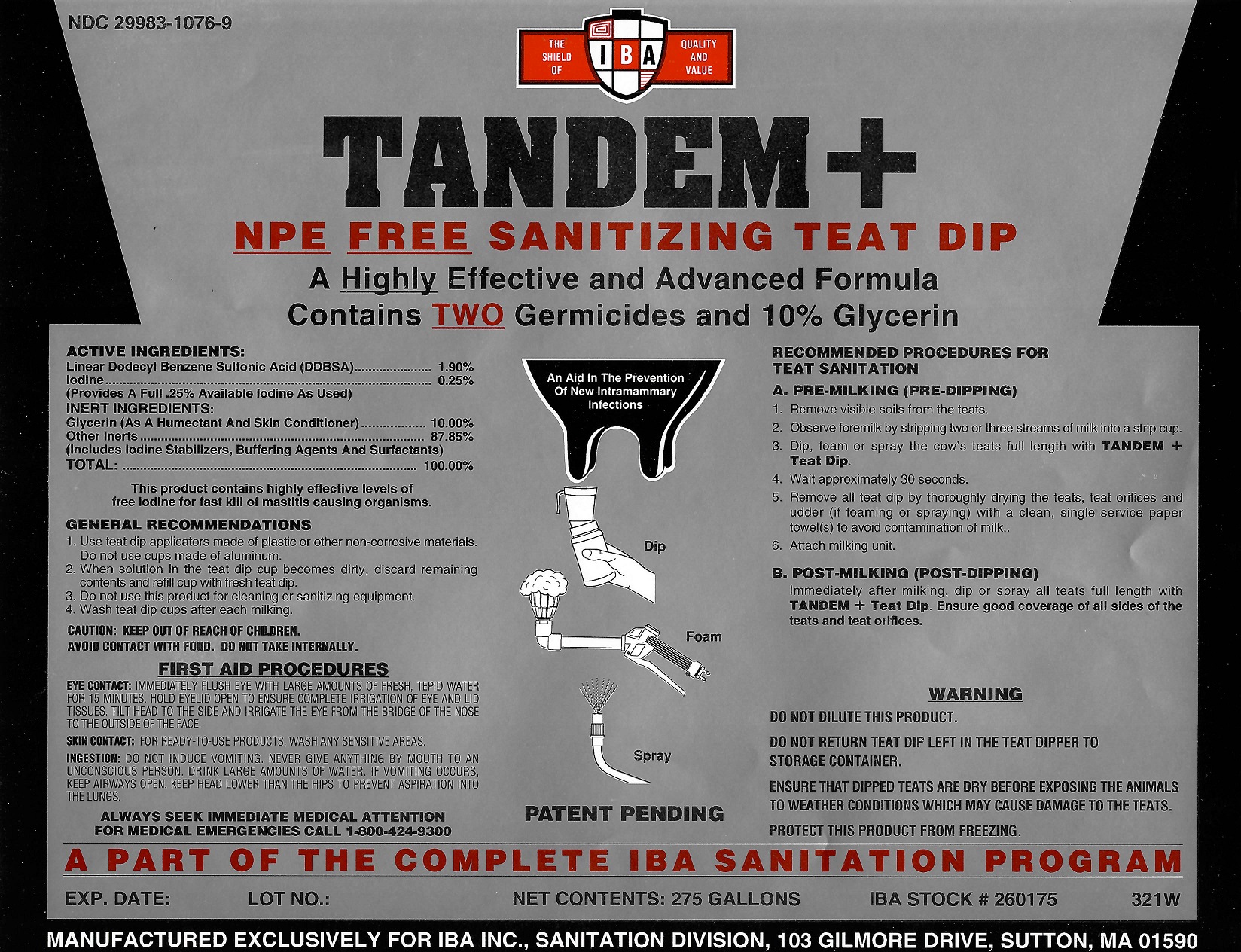 DRUG LABEL: Tandem Plus NPE Free
NDC: 29983-1076 | Form: LIQUID
Manufacturer: IBA
Category: animal | Type: OTC ANIMAL DRUG LABEL
Date: 20251211

ACTIVE INGREDIENTS: DODECYLBENZENESULFONIC ACID 1.9 kg/100 kg; IODINE 0.25 kg/100 kg

Tandem Plus NPE Free

ACTIVE INGREDIENTS

Linear Dodecyl Benzene Sulfonic Acid (DDBSA)....... 1.90%

Iodine............................................................... 0.25%

(Provides a full 0.25% Available Iodine as used)

INERT INGREDIENTS:

Glycerine (as a humectant and skin conditioner) ..... 10.00%

Other inerts: .............................................. ........87.85%

(Includes Iodine Stabilizers, Buffering Agents, and Surfactants)
TOTAL: ............................................................. 100.00%

This product contains highly effective levels of
free iodine for fast kill of mastitis causing organisms.

RECOMMENDED PROCEDURES FOR TEAT SANITATION

A. Pre-Milking (Pre-dipping)

1. Remove visible solids from the teats.

2. Observe foremilk by stripping two or three streams of milk into a strip cup

3. Dip, foam or spray the cow's teats full length with TANDEM + Teat Dip

4.Wait approximately 30 seconds

5. Remove all teat dip thoroughly dryin the teats, teat orifices and udder (if foaming or spraying) with a clean, single service paper towel(s) to avoid contamination of milk.

6. Attach milking unit.
B. POST-MILKING (POST-DIPPING)
Immediately after milking dip or spray all teats full length with TANDEM + Teat Dip. Ensure good coverage of all sides of the teats and teat orifices.

GENERAL RECOMMENDATIONS
1. Use teat dip applicators made of plastic or other non-corrosive materials. Do not use cups made of aluminum.
2. When solution in the teat dip cup becomes dirty, discard remaining contents and refill cup with fresh teat dip.
3. Do not use this product for cleaning or sanitizing equipment
4. Wash Teat Dip cups after each milking.

WARNING

DO NOT DILUTE THIS PRODUCT.

DO NOT RETURN TEAT DIP LEFT IN THE TEAT DIPPER TO STORAGE CONTAINER.

ENSURE THAT DIPPED TEATS ARE DRY BEFORE EXPOSING THE ANIMALS TO WEATHER CONDITIONS WHICH MAY CAUSE DAMAGE TO THE TEATS.
PROTECT THIS PRODUCT FROM FREEZING.

NOT FOR HUMAN USE.

CAUTION: KEEP OUT OF REACH OF CHILDREN.
AVOID CONTACT WITH FOOD. DO NOT TAKE INTERNALLY.

FIRST AID PROCEDURES

EYE CONTACT: IMMEDIATELY FLUSH EYE WITH LARGE AMOUNTS OF FRESH, TEPID WATER FOR 15 MINUTES. HOLD EYELID OPEN TO ENSURE COMPLETE IRRIGATION OF EYE AND LID TISSUES. TILT HEAD TO THE SIDE AND IRRIGATE THE EYE FROM THE BRIDGE OF THE NOSE TO THE OUTSIDE OF THE FACE.
SKIN CONTACT: FOR READY-TO-USE PRODUCTS. WASH ANY SENSITIVE AREAS.
INGESTION:DO NOT INDUCE VOMITING. NEVER GIVE ANYTHING BY MOUTH TO AN UNCONSCIOUS PERSON. DRINK LARGE AMOUNTS OF WATER. IF VOMITING OCCURS KEEP AIRWAYS OPEN. KEEP HEAD LOWER THAN THE HIPS TO PREVENT ASPIRATION INTO THE LUNGS.

ALWAYS SEEK IMMEDIATE MEDICAL ATTENTION
FOR MEDICAL EMERGENCIES CALL 1-800-424-9300